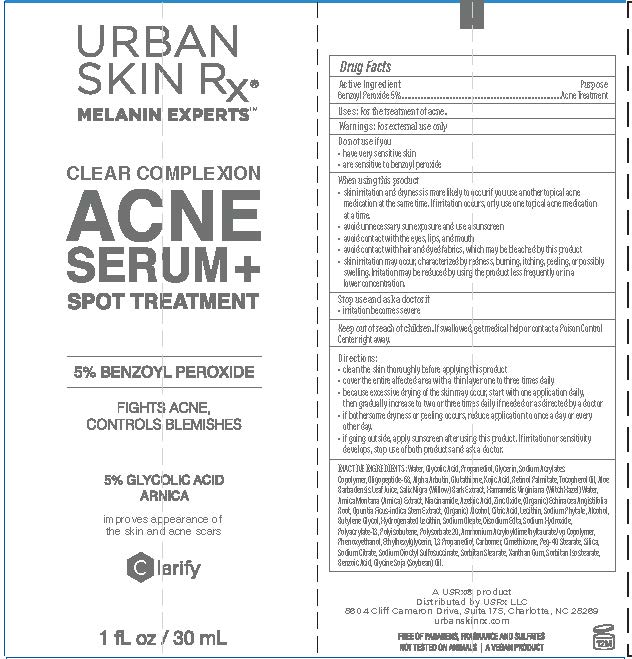 DRUG LABEL: Clear Complexion Acne Serum
NDC: 70809-1903 | Form: CREAM
Manufacturer: USRX LLC
Category: otc | Type: HUMAN OTC DRUG LABEL
Date: 20241001

ACTIVE INGREDIENTS: BENZOYL PEROXIDE 7.5 mg/100 mL
INACTIVE INGREDIENTS: GLYCOLIC ACID; PROPANEDIOL; GLYCERIN; WATER

Clear Complexion Acne Serum

PACKAGE LABEL

ACTIVE INGREDIENT

Benzoyl Peroxide 7.5%

PURPOSE

Acne Treatment

WARNINGS

- Warning For external use only
- When using this product avoid contact with eyes. If contact occurs, flush thoroughly with water.
- Stop and ask a doctor if rash or irritation develops and lasts.

DOSAGE AND ADMINISTRATION

Directions: Thoroughly cleanse face and pat dry. Apply to face and neck area for an all over acne treatment or apply directly to the breakout/pimple for a fast acting spot treatment. Can be used 1-2 times daily or for sensitive skin types use every other night. If dryness or irritation occurs, reduce amount of applications.

INACTIVE INGREDIENT

WATER, GLYCOLIC ACRYLATESCOPOLYMER, OLIGOPEPTI KOJICACID, RETINOLPALMITATE, TOCO JUICE, SALIXNIGRA(WILLOW) BARKEX HAZEL) WATER, ARNICAMONTANA(AR ACID, ZINC OXIDE, (ORGANIC) ECHI FICUS-INDICASTEMEXTRACT, (ORGA SODIUMPHYTATE, ALCOHOL, BUTYLEN SODIUMOLEATE, DISODIUMEDTA, SO POLYISOBUTENE, POLYSORBATE20, AM COPOLYMER, PHENOXYETHANOL, ETH CARBOMER, DIMETHICONE, PEG-40 SODIUM DIOCTYL SULFOSUCCINATE, SORBITAN ISOSTEARATE, BENZOIC A
ACID, PROPANEDIOL, GLYCERIN, SODIUM DE-68, ALPHA-ARBUTIN, GLUTATHIONE, PHEROLOIL, ALOEBARBADENSISLEAF TRACT, HAMAMELISVIRGINIANA(WITCH NICA) EXTRACT, NIACINAMIDE, AZELAIC NACEAANGISTIFOLIAROOT, OPUNTIA NIC) ALCOHOL, CITRICACID, LECITHIN, EGLYCOL, HYDROGENATEDLECITHIN, DIUMHYDROXIDE, POLYACRYLATE-13, MONIUMACRYLOYLDIMETHYLTAURATE/VP YLHEXYLGLYCERIN, 1,3PROPANEDIOL, STEARATE, SILICA, SODIUM CITRATE, SORBITAN STEARATE, XANTHAN GUM,
CID, GLYCINE SOJA (SOYBEAN) OIL.